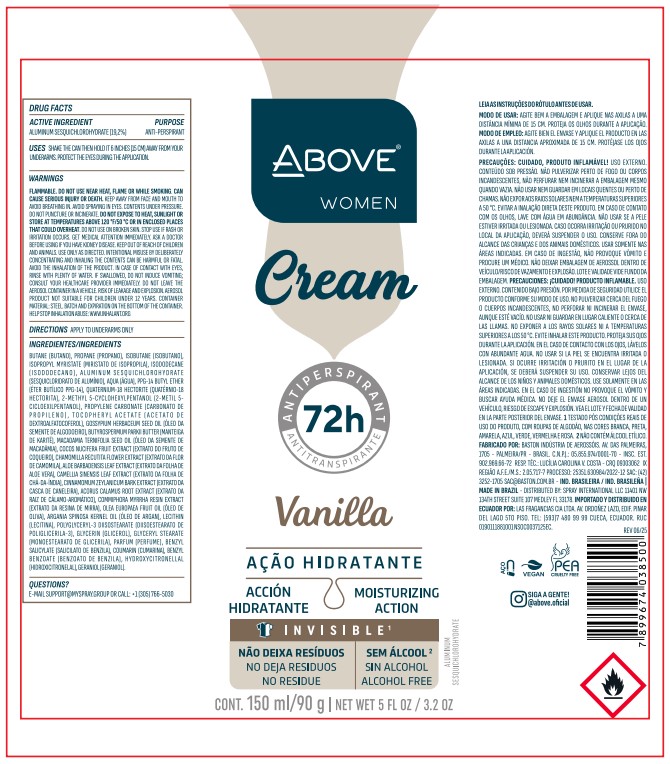 DRUG LABEL: ABOVE  WOMEN VANILLA
NDC: 73306-1182 | Form: CREAM
Manufacturer: BASTON INDUSTRIA DE AEROSSOIS LTDA
Category: otc | Type: HUMAN OTC DRUG LABEL
Date: 20260218

ACTIVE INGREDIENTS: ALUMINUM SESQUICHLOROHYDRATE 19.2 mg/90 g
INACTIVE INGREDIENTS: ISOBUTANE

ABOVE CREAM WOMEN VANILLA ANTIPERSPIRANT DEODORANT 72H

ALUMINUM SESQUICHLOROHYDRATE

ALUMINUM SESQUICHLOROHYDRATE ANTIPERSPIRANT

ALUMINUM SESQUICHLOROHYDRATE
ANTIPERSPIRANT

Shake the can and hold it 15 cm (6 inches) away from your armpits. Avoid contact with your eyes during application. Apply only to the underarms.

Shake the can and hold it 15 cm (6 inches) away from your armpits. Avoid contact with your eyes during application.
Apply only to the underarms.

SUPPORT@MYSPRAY.GROUP OR CALL (305) 766-5030

FLAMMABLE. DO NOT USE NEAR HEAT, FLAME OR WHILE SMOKING. CAN CAUSE SERIOUS INJURY OR DEATH. KEEP AWAY FROM FACE AND MOUTH TO AVOID BREATHING IN. AVOID SPRAYING IN EYES. CONTENTS UNDER PRESSURE. DO NOT PUNCTURE OR INCINERATE. DO NOT EXPOSE TO HEAT, SUNLIGHT OR STORE AT TEMPERATURES ABOVE 120°F/50°C OR IN ENCLOSED PLACES THAT COULD OVERHEAT. DO NOT USE ON BROKEN SKIN. STOP USE IF RASH OR IRRITATION OCCURS. GET MEDICAL ATTENTION IMMEDIATELY. ASK A DOCTOR BEFORE USING IF YOU HAVE KIDNEY DISEASE. KEEP OUT OF REACH OF CHILDREN AND ANIMALS. USE ONLY AS DIRECTED. INTENTIONAL MISUSE BY DELIBERATELY CONCENTRATING AND INHALING THE CONTENTS CAN BE HARMFUL OR FATAL. AVOID THE INHALATION OF THE PRODUCT. IN CASE OF CONTACT WITH EYES, RINSE WITH PLENTY OF WATER. IF SWALLOWED, DO NOT INDUCE VOMITING; CONSULT YOUR HEALTHCARE PROVIDER IMMEDIATELY. DO NOT LEAVE THE AEROSOL CONTAINER IN A VEHICLE. RISK OF LEAKAGE AND EXPLOSION. CONTAINER MATERIAL: STEEL. BATCH AND EXPIRATION ON THE BOTTOM OF THE CONTAINER. HELP STOP INHALATION ABUSE: WWW.INHALANT.ORG

FLAMMABLE. DO NOT USE NEAR HEAT, FLAME OR WHILE SMOKING.
CAN CAUSE SERIOUS INJURY OR DEATH. KEEP AWAY FROM FACE AND
MOUTH TO AVOID BREATHING IN. AVOID SPRAYING IN EYES. CONTENTS
UNDER PRESSURE. DO NOT PUNCTURE OR INCINERATE. DO NOT EXPOSE
TO HEAT, SUNLIGHT OR STORE AT TEMPERATURES ABOVE 120°F/50°C
OR IN ENCLOSED PLACES THAT COULD OVERHEAT. DO NOT USE ON
BROKEN SKIN. STOP USE IF RASH OR IRRITATION OCCURS. GET MEDICAL
ATTENTION IMMEDIATELY. ASK A DOCTOR BEFORE USING IF YOU HAVE
KIDNEY DISEASE. KEEP OUT OF REACH OF CHILDREN AND ANIMALS. USE
ONLY AS DIRECTED. INTENTIONAL MISUSE BY DELIBERATELY
CONCENTRATING AND INHALING THE CONTENTS CAN BE HARMFUL OR
FATAL. AVOID THE INHALATION OF THE PRODUCT. IN CASE OF CONTACT
WITH EYES, RINSE WITH PLENTY OF WATER. IF SWALLOWED, DO NOT
INDUCE VOMITING; CONSULT YOUR HEALTHCARE PROVIDER IMMEDIATELY.
DO NOT LEAVE THE AEROSOL CONTAINER IN A VEHICLE. RISK OF LEAKAGE
AND EXPLOSION. CONTAINER MATERIAL: STEEL. BATCH AND EXPIRATION ON
THE BOTTOM OF THE CONTAINER. HELP STOP INHALATION ABUSE:
WWW.INHALANT.ORG

KEEP OUT OF REACH OF CHILDREN

UNDERARM ANTIPERSPIRANT DEODORANT

FLAMMABLE. DO NOT USE NEAR HEAT, FLAME OR WHILE SMOKING. CAN CAUSE SERIOUS INJURY OR DEATH. KEEP AWAY FROM FACE AND MOUTH TO AVOID BREATHING IN. AVOID SPRAYING IN EYES. CONTENTS UNDER PRESSURE. DO NOT PUNCTURE OR INCINERATE. DO NOT EXPOSE TO HEAT, SUNLIGHT OR STORE AT TEMPERATURES ABOVE 120°F/50°C OR IN ENCLOSED PLACES THAT COULD OVERHEAT. DO NOT USE ON BROKEN SKIN. STOP USE IF RASH OR IRRITATION OCCURS. GET MEDICAL ATTENTION IMMEDIATELY. ASK A DOCTOR BEFORE USING IF YOU HAVE KIDNEY DISEASE. KEEP OUT OF REACH OF CHILDREN AND ANIMALS. USE ONLY AS DIRECTED. INTENTIONAL MISUSE BY DELIBERATELY CONCENTRATING AND INHALING THE CONTENTS CAN BE HARMFUL OR FATAL. AVOID THE INHALATION OF THE PRODUCT. IN CASE OF CONTACT WITH EYES, RINSE WITH PLENTY OF WATER. IF SWALLOWED, DO NOT INDUCE VOMITING; CONSULT YOUR HEALTHCARE PROVIDER IMMEDIATELY. DO NOT LEAVE THE AEROSOL CONTAINER IN A VEHICLE. RISK OF LEAKAGE AND EXPLOSION. CONTAINER MATERIAL: STEEL. BATCH AND EXPIRATION ON THE BOTTOM OF THE CONTAINER. HELP STOP INHALATION ABUSE: WWW.INHALANT.ORG

FLAMMABLE. DO NOT USE NEAR HEAT, FLAME OR WHILE SMOKING.
CAN CAUSE SERIOUS INJURY OR DEATH. KEEP AWAY FROM FACE AND
MOUTH TO AVOID BREATHING IN. AVOID SPRAYING IN EYES. CONTENTS
UNDER PRESSURE. DO NOT PUNCTURE OR INCINERATE. DO NOT EXPOSE
TO HEAT, SUNLIGHT OR STORE AT TEMPERATURES ABOVE 120°F/50°C
OR IN ENCLOSED PLACES THAT COULD OVERHEAT. DO NOT USE ON
BROKEN SKIN. STOP USE IF RASH OR IRRITATION OCCURS. GET MEDICAL
ATTENTION IMMEDIATELY. ASK A DOCTOR BEFORE USING IF YOU HAVE
KIDNEY DISEASE. KEEP OUT OF REACH OF CHILDREN AND ANIMALS. USE
ONLY AS DIRECTED. INTENTIONAL MISUSE BY DELIBERATELY
CONCENTRATING AND INHALING THE CONTENTS CAN BE HARMFUL OR
FATAL. AVOID THE INHALATION OF THE PRODUCT. IN CASE OF CONTACT
WITH EYES, RINSE WITH PLENTY OF WATER. IF SWALLOWED, DO NOT
INDUCE VOMITING; CONSULT YOUR HEALTHCARE PROVIDER IMMEDIATELY.
DO NOT LEAVE THE AEROSOL CONTAINER IN A VEHICLE. RISK OF LEAKAGE
AND EXPLOSION. CONTAINER MATERIAL: STEEL. BATCH AND EXPIRATION ON
THE BOTTOM OF THE CONTAINER. HELP STOP INHALATION ABUSE:
WWW.INHALANT.ORG

BUTANE, PROPANE, ISOBUTANE, ISOPROPYL MYRISTATE, ISODODECANE, PARFUM (ALERGENOS: BENZYL SALICYLATE, COUMARIN, BENZYL BENZOATE, HYDROXYCITRONELLAL, GERANIOL), AQUA, PPG-14 BUTYL ETHER, QUATERNIUM-18 HECTORITE, 2-METHYL 5-CYCLOHEXYLPENTANOL, PROPYLENE CARBONATE, TOCOPHERYL ACETATE, GOSSYPIUM HERBACEUM SEED OIL, BUTYROSPERMUM PARKII BUTTER, MACADAMIA TERNIFOLIA SEED OIL, COCOS NUCIFERA FRUIT EXTRACT, CHAMOMILLA RECUTITA FLOWER EXTRACT, ALOE BARBADENSIS LEAF EXTRACT, CAMELLIA SINENSIS LEAF EXTRACT, CINNAMOMUM ZEYLANICUM BARK EXTRACT, ACORUS CALAMUS ROOT EXTRACT, COMMIPHORA MYRRHA RESIN EXTRACT, OLEA EUROPAEA FRUIT OIL, ARGANIA SPINOSA KERNEL OIL, LECITHIN, POLYGLYCERYL-3 DIISOSTEARATE, GLYCERIN, GLYCERYL STEARATE